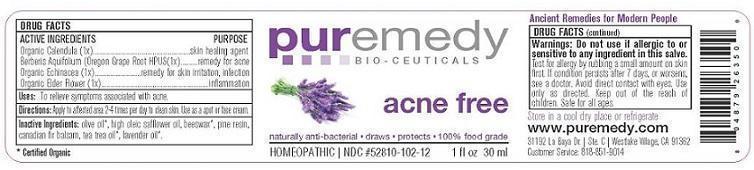 DRUG LABEL: ACNE FREE
NDC: 52810-102 | Form: SALVE
Manufacturer: PUREMEDY
Category: homeopathic | Type: HUMAN OTC DRUG LABEL
Date: 20240111

ACTIVE INGREDIENTS: ECHINACEA ANGUSTIFOLIA 1 [hp_X]/100 mL; CALENDULA OFFICINALIS FLOWER 1 [hp_X]/100 mL; SAMBUCUS NIGRA FLOWER 1 [hp_X]/100 mL; MAHONIA AQUIFOLIUM FRUITING TOP 1 [hp_X]/100 mL
INACTIVE INGREDIENTS: OLIVE OIL; SAFFLOWER OIL; YELLOW WAX; PINE NEEDLE OIL (PINUS SYLVESTRIS); CANADA BALSAM; TEA TREE OIL; LAVANDULA ANGUSTIFOLIA FLOWER

ACNE FREE (52810-102)

ACTIVE INGREDIENTS

ECHINACEA ANGUSTIFOLIA (2X) HPUS (ECHINACEA)

SAMBUCUS NIGRA (2X) HPUS (ELDERBERRY)

ORGANIC CALENDULA OFFICINALIS (2X) HPUS (MARIGOLD)

PINUS SILVESTRIS (1X) HPUS (PINE RESIN)

PURPOSE

PROPERTIES

ACNE TREATMENT

SKIN PROTECTANT

SKIN PROTECTANT

SKIN PROTECTANT

INDICATIONS AND USAGE

USES: TO RELIEVE SYMPTOMS ASSOCIATED WITH ACNE

DOSAGE AND ADMINISTRATION

DIRECTIONS: APPLY LIBERALLY TO AFFECTED AREA 2-4 TIMES PER DAY OR AS NEEDED. MAY BE USED AS A FACE CREAM OR SPOT TREATMENT.

INACTIVE INGREDIENT

OTHER INGREDIENTS: ORGANIC EXTRA VIRGIN OLIVE OIL, ORGANIC SAFFLOWER OIL, ORGANIC BEESWAX, CANADIAN FIR BALSAM, ORGANIC TEA TREE OIL.

WARNINGS

WARNING: TEST FOR ALLERGY BY RUBBING A SMALL AMOUNT ON SKIN FIRST. DO NOT USE IF ALLERGIC TO OR HYPER-SENSITIVE TO ANY INGREDIENT IN THIS SALVE. IF CONDITION PERSISTS OR WORSENS CONSULT YOUR HEALTH CARE PROVIDER.

KEEP OUT OF REACH OF CHILDREN.

OTHER SAFETY INFORMATION

STORE IN A COOL DRY PLACE OR REFRIGERATE